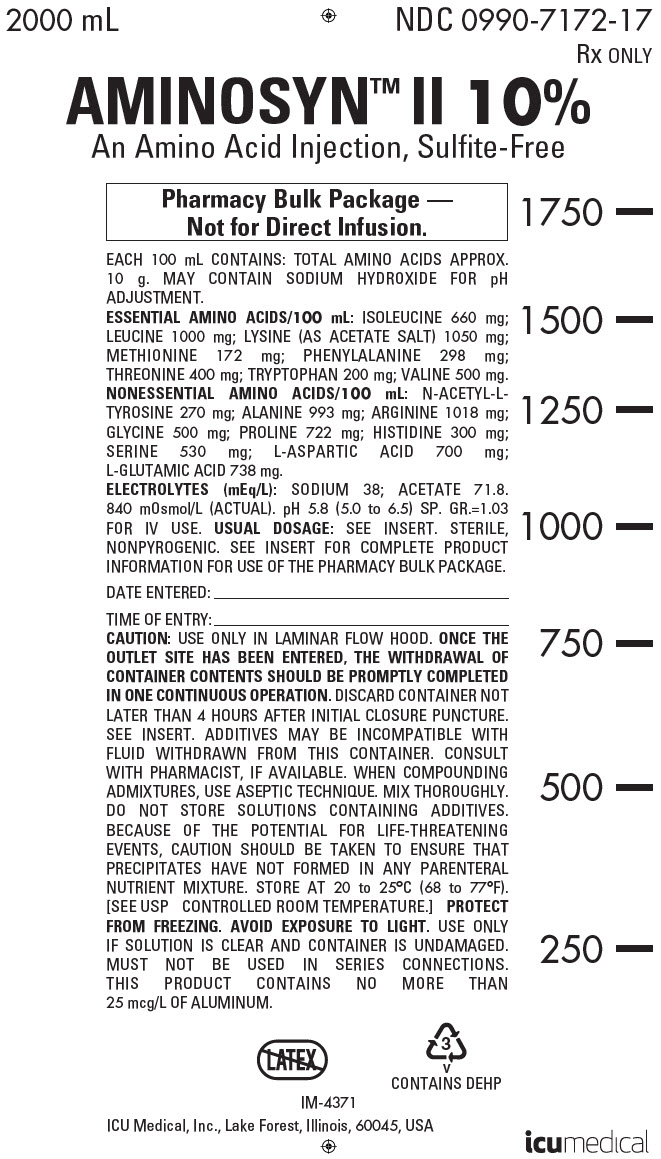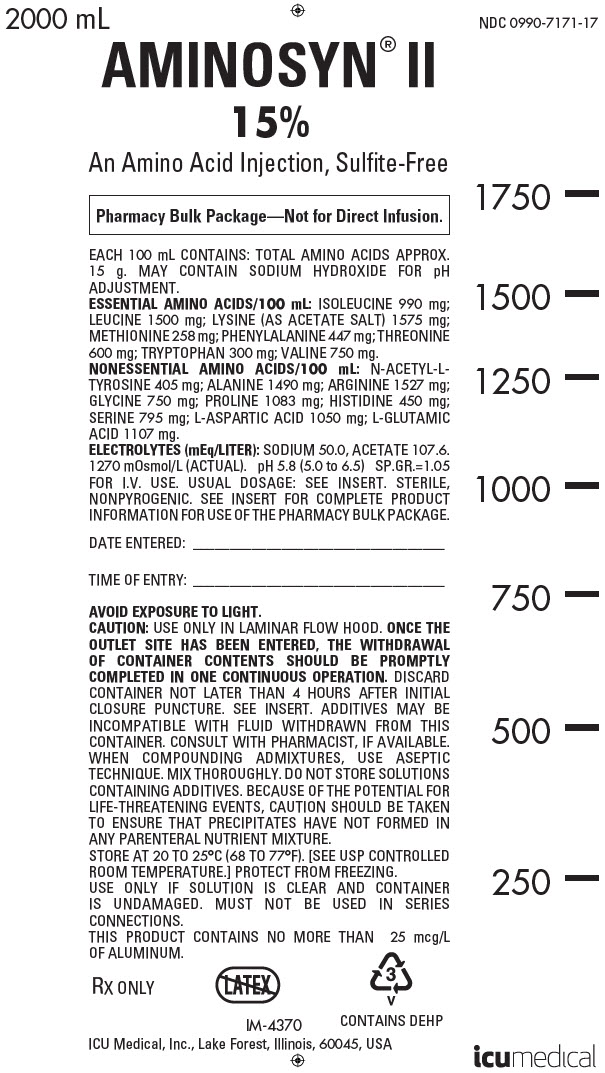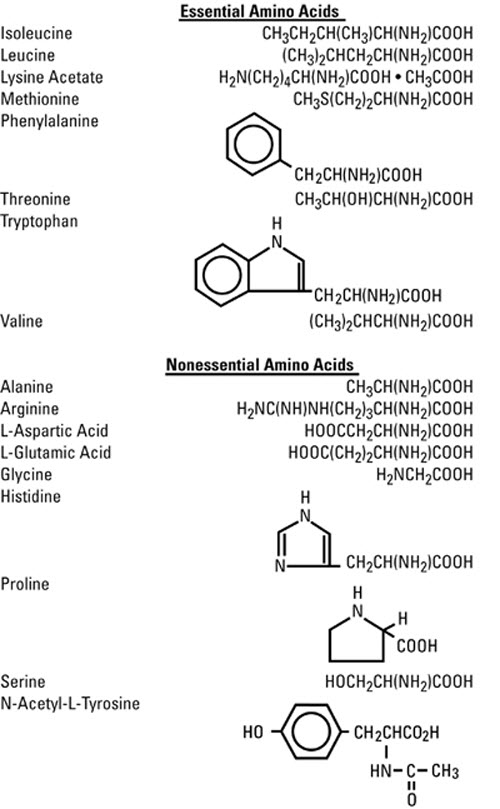 DRUG LABEL: Aminosyn II
NDC: 0990-7172 | Form: INJECTION, SOLUTION
Manufacturer: ICU Medical Inc.
Category: prescription | Type: HUMAN PRESCRIPTION DRUG LABEL
Date: 20251102

ACTIVE INGREDIENTS: ISOLEUCINE 660 mg/100 mL; LEUCINE 1000 mg/100 mL; LYSINE ACETATE 1050 mg/100 mL; METHIONINE 172 mg/100 mL; PHENYLALANINE 298 mg/100 mL; THREONINE 400 mg/100 mL; TRYPTOPHAN 200 mg/100 mL; VALINE 500 mg/100 mL; ALANINE 993 mg/100 mL; ARGININE 1018 mg/100 mL; ASPARTIC ACID 700 mg/100 mL; GLUTAMIC ACID 738 mg/100 mL; HISTIDINE 300 mg/100 mL; PROLINE 722 mg/100 mL; SERINE 530 mg/100 mL; ACETYL L-TYROSINE 270 mg/100 mL; GLYCINE 500 mg/100 mL
INACTIVE INGREDIENTS: SODIUM HYDROXIDE

AminosynTM II

AN AMINO ACID INJECTION, Sulfite-Free

BOXED WARNING

Pharmacy Bulk Package – Not For Direct Infusion.

Flexible Plastic Container

Rx only

DESCRIPTION

Aminosyn™ II, Sulfite-Free, (an amino acid injection) is a sterile, nonpyrogenic solution for intravenous infusion. Aminosyn II is oxygen sensitive. The Pharmacy Bulk Package is a sterile dosage form which contains multiple single doses for use only in a pharmacy bulk admixture program. The formulations are described below:

Essential Amino Acids (mg/100 mL) |  | Aminosyn II
 |  | 10% | 15%
Isoleucine |  | 660 | 990
Leucine |  | 1000 | 1500
Lysine (acetate)* |  | 1050 | 1575
Methionine |  | 172 | 258
Phenylalanine |  | 298 | 447
Threonine |  | 400 | 600
Tryptophan |  | 200 | 300
Valine |  | 500 | 750
*Amount cited is for lysine alone and does not include the acetate.
Nonessential Amino Acids (mg/100 mL)
Alanine |  | 993 | 1490
Arginine |  | 1018 | 1527
L-Aspartic Acid |  | 700 | 1050
L-Glutamic Acid |  | 738 | 1107
Histidine |  | 300 | 450
Proline |  | 722 | 1083
Serine |  | 530 | 795
N-Acetyl-L-Tyrosine |  | 270 | 405
Glycine |  | 500 | 750
Other Characteristics
Protein Equivalent | (approx. grams/liter) | 100 | 150
Total Nitrogen | (grams/liter) | 15.3 | 23.0
Osmolarity | (mOsmol/liter, actual) | 840 | 1270
pHa |  | 5.8 (5.0 – 6.5) | 5.8 (5.0 – 6.5)
Specific Gravity |  | 1.03 | 1.05
Electrolytes | (mEq/L)
Sodium | (Na^+)b | 38 | 50
Acetate | (C2H3O2^-)c | 71.8 | 107.6
a Solution contains sodium hydroxide for pH adjustment.; b Figure includes Na^+ from the pH adjustor.; c Includes acetate from lysine acetate.

The flexible plastic container is fabricated from a specially formulated polyvinylchloride. Water can permeate from inside the container into the overwrap but not in amounts to affect the solution significantly. Solutions in contact with the plastic container may leach out certain chemical components from the plastic in very small amounts; however, biological testing was supportive of the safety of the plastic container materials.

Exposure to temperatures above 25°C/77°F during transport and storage will lead to minor losses in moisture content. Higher temperatures lead to greater losses. It is unlikely that these minor losses will lead to clinically significant changes within the expiration period.

The formulas for the individual amino acids are as follows:

The Pharmacy Bulk Package is designed for use with manual, gravity flow operations and automated compounding devices for preparing sterile parenteral nutrient admixtures; it contains no bacteriostat. Multiple single doses may be dispensed during continual aliquoting operations. Withdrawal of container contents should be promptly completed within 4 hours after initial closure puncture.

CLINICAL PHARMACOLOGY

Aminosyn II, Sulfite-Free, (an amino acid injection) provides crystalline amino acids to promote protein synthesis and wound healing, and to reduce the rate of endogenous protein catabolism. Aminosyn II, given by central venous infusion in combination with concentrated dextrose, electrolytes, vitamins, trace metals, and ancillary fat supplements, constitutes total parenteral nutrition (TPN). Aminosyn II can also be administered by peripheral vein with dextrose and maintenance electrolytes. Intravenous fat emulsion may be substituted for part of the carbohydrate calories during either TPN or peripheral vein administration of Aminosyn II.

INDICATIONS AND USAGE

Aminosyn II, Sulfite-Free, (an amino acid injection) infused with dextrose by peripheral vein infusion is indicated as a source of nitrogen in the nutritional support of patients with adequate stores of body fat, in whom, for short periods of time, oral nutrition cannot be tolerated, is undesirable, or inadequate.

SUPPLEMENTAL ELECTROLYTES, IN ACCORDANCE WITH THE PRESCRIPTION OF THE ATTENDING PHYSICIAN, MUST BE ADDED TO AMINOSYN II SOLUTIONS WITHOUT ELECTROLYTES.

Aminosyn II can be administered peripherally with dilute (5 to 10%) dextrose solution and I.V. fat emulsion as a source of nutritional support. This form of nutritional support can help to preserve protein and reduce catabolism in stress conditions where oral intake is inadequate.

Aminosyn II is also indicated for central vein infusion to prevent or reverse negative nitrogen balance in patients where the alimentary tract, by the oral, gastrostomy or jejunostomy route cannot or should not be used and gastrointestinal absorption of protein is impaired.

CONTRAINDICATIONS

This preparation should not be used in patients with hepatic coma or metabolic disorders involving impaired nitrogen utilization.

WARNINGS

Intravenous infusion of amino acids may induce a rise in blood urea nitrogen (BUN), especially in patients with impaired hepatic or renal function. Appropriate laboratory tests should be performed periodically and infusion discontinued if BUN levels exceed normal postprandial limits and continue to rise. It should be noted that a modest rise in BUN normally occurs as a result of increased protein intake.

Administration of amino acid solutions to a patient with hepatic insufficiency may result in serum amino acid imbalances, metabolic alkalosis, prerenal azotemia, hyperammonemia, stupor and coma.

Administration of amino acid solutions in the presence of impaired renal function may augment an increasing BUN, as does any protein dietary component.

Solutions containing sodium ion should be used with great care, if at all, in patients with congestive heart failure, severe renal insufficiency and in clinical states in which there exists edema with sodium retention.

Solutions which contain potassium ion should be used with great care, if at all, in patients with hyperkalemia, severe renal failure and in conditions in which potassium retention is present.

Solutions containing acetate ion should be used with great care in patients with metabolic or respiratory alkalosis. Acetate should be administered with great care in those conditions in which there is an increased level or an impaired utilization of this ion, such as severe hepatic insufficiency.

Hyperammonemia is of special significance in infants, as it can result in mental retardation. Therefore, it is essential that blood ammonia levels be measured frequently in infants.

Instances of asymptomatic hyperammonemia have been reported in patients without overt liver dysfunction. The mechanisms of this reaction are not clearly defined, but may involve genetic defects and immature or subclinically impaired liver function.

WARNING: This product contains aluminum that may be toxic. Aluminum may reach toxic levels with prolonged parenteral administration if kidney function is impaired. Premature neonates are particularly at risk because their kidneys are immature, and they require large amounts of calcium and phosphate solutions, which contain aluminum.

Research indicates that patients with impaired kidney function, including premature neonates, who receive parenteral levels of aluminum at greater than 4 to 5 mcg/kg/day accumulate aluminum at levels associated with central nervous system and bone toxicity. Tissue loading may occur even at lower rates of administration.

PRECAUTIONS

Special care must be taken when administering glucose to provide calories in diabetic or prediabetic patients.

Feeding regimens which include amino acids should be used with caution in patients with history of renal disease, pulmonary disease, or with cardiac insufficiency so as to avoid excessive fluid accumulation.

The effect of infusion of amino acids, without dextrose, upon carbohydrate metabolism of children is not known at this time.

Nitrogen intake should be carefully monitored in patients with impaired renal function.

For long-term total nutrition, or if a patient has inadequate fat stores, it is essential to provide adequate exogenous calories concurrently with the amino acids. Concentrated dextrose solutions are an effective source of such calories. Such strongly hypertonic nutrient solutions should be administered through an indwelling intravenous catheter with the tip located in the superior vena cava.

SPECIAL PRECAUTIONS FOR CENTRAL VENOUS INFUSIONS

ADMINISTRATION BY CENTRAL VENOUS CATHETER SHOULD BE USED ONLY BY THOSE FAMILIAR WITH THIS TECHNIQUE AND ITS COMPLICATIONS.

Central vein infusion (with added concentrated carbohydrate solutions) of amino acid solutions requires a knowledge of nutrition as well as clinical expertise in recognition and treatment of complications. Attention must be given to solution preparation, administration and patient monitoring. IT IS ESSENTIAL THAT A CAREFULLY PREPARED PROTOCOL BASED ON CURRENT MEDICAL PRACTICES BE FOLLOWED, PREFERABLY BY AN EXPERIENCED TEAM.

SUMMARY HIGHLIGHTS OF COMPLICATIONS (consult current medical literature).

1. Technical:
  The placement of a central venous catheter should be regarded as a surgical procedure. One should be fully acquainted with various techniques of catheter insertion. For details of technique and placement sites, consult the medical literature. X-ray is the best means of verifying catheter placement. Complications known to occur from the placement of central venous catheters are pneumothorax, hemothorax, hydrothorax, artery puncture and transection, injury to the brachial plexus, malposition of the catheter, formation of arteriovenous fistula, phlebitis, thrombosis and air and catheter emboli.
2. Septic:
  The constant risk of sepsis is present during administration of total parenteral nutrition. It is imperative that the preparation of the solution and the placement and care of catheters be accomplished under strict aseptic conditions.
  Solutions should ideally be prepared in the hospital pharmacy in a laminar flow hood using careful aseptic technique to avoid inadvertent touch contamination. Solutions should be used promptly after mixing. Storage should be under refrigeration and limited to a brief period of time, preferably less than 24 hours.
  Administration time for a single container and set should never exceed 24 hours.
3. Metabolic:
  The following metabolic complications have been reported with TPN administration: metabolic acidosis and alkalosis, hypophosphatemia, hypocalcemia, osteoporosis, glycosuria, hyperglycemia, hyperosmolar nonketotic states and dehydration, rebound hypoglycemia, osmotic diuresis and dehydration, elevated liver enzymes, hypo- and hypervitaminosis, electrolyte imbalances and hyperammonemia in pediatric patients. Frequent evaluations are necessary especially during the first few days of therapy to prevent or minimize these complications.
  Administration of glucose at a rate exceeding the patient’s utilization rate may lead to hyperglycemia, coma and death.

Carcinogenesis, Mutagenesis, Impairment of Fertility:

Studies with solutions from flexible plastic containers have not been performed to evaluate carcinogenic potential, mutagenic potential or effects on fertility.

PREGNANCY

Pregnancy Category C. Animal reproduction studies have not been conducted with Aminosyn II (an amino acid injection). It is not known whether Aminosyn II can cause fetal harm when administered to a pregnant woman or can affect reproduction capacity. Aminosyn II should be given to a pregnant woman only if clearly needed.

Nursing Mothers:

Caution should be exercised when solutions from flexible plastic containers are administered to a nursing mother.

Geriatric Use:

Clinical Studies of Aminosyn II have not been performed to determine whether patients over 65 years of age respond differently from younger subjects. Other reported clinical experience has not identified differences in responses between elderly and younger patients. In general, dose selection for an elderly patient should be cautious, reflecting the greater frequency of decreased hepatic, renal, or cardiac function, and of concomitant disease or other drug therapy. This drug is known to be substantially excreted by kidney, and the risk for adverse reactions to this drug may be greater in patients with impaired renal function. Because elderly patients are more likely to have decreased renal function, care should be taken in dose selection, and it may be useful to monitor renal function.

Pediatric Use:

Safety and effectiveness of solutions from flexible plastic containers in pediatric patients have not been well established.

CLINICAL EVALUATION AND LABORATORY DETERMINATIONS, AT THE DISCRETION OF THE ATTENDING PHYSICIAN, ARE NECESSARY FOR PROPER MONITORING DURING ADMINISTRATION. Do not withdraw venous blood for blood chemistries through the peripheral infusion site, as interference with estimations of nitrogen containing substances may occur. Blood studies should include glucose, urea nitrogen, serum electrolytes, ammonia, cholesterol, acid-base balance, serum proteins, kidney and liver function tests, osmolarity and hemogram. White blood count and blood cultures are to be determined if indicated. Urinary osmolality and glucose should be determined as necessary.

Drug Interactions

Because of its antianabolic activity, concurrent administration of tetracycline may reduce the potential effects of amino acids infused with dextrose as part of a parenteral feeding regimen.

ADVERSE REACTIONS

Peripheral Infusions

A 3.5% to 5% solution of amino acids (without additives) is slightly hypertonic. Use of large peripheral veins, inline filters, and slowing the rate of infusion may reduce the incidence of local venous irritation. Electrolyte additives should be spread throughout the day. Irritating additive medications may need to be infused at another venous site.

Generalized flushing, fever and nausea also have been reported during peripheral infusions of amino acid solutions.

OVERDOSAGE

In the event of overhydration or solute overload, re-evaluate the patient and institute appropriate corrective measures. (See WARNINGS and PRECAUTIONS.)

DOSAGE AND ADMINISTRATION

Each 100 mL of Aminosyn II contains:

 | Amino Acids | Nitrogen
Aminosyn II 10% | 10 g | 1.53 g
Aminosyn II 15% | 15 g | 2.30 g

The total daily dose of the solution depends on the daily protein requirements and on the patient’s metabolic and clinical response. In many patients, provision of adequate calories in the form of hypertonic dextrose may require the administration of exogenous insulin to prevent hyperglycemia and glycosuria. To prevent rebound hypoglycemia, a solution containing 5% dextrose should be administered when hypertonic dextrose infusions are abruptly discontinued.

Parenteral drug products should be inspected visually for particulate matter and discoloration prior to administration, whenever solution and container permit. COLOR VARIATION FROM PALE YELLOW TO YELLOW IS NORMAL AND DOES NOT ALTER EFFICACY.

Some opacity of the plastic due to moisture absorption during the sterilization process may be observed. This is normal and does not affect the solution quality or safety. The opacity will diminish gradually.

Aminosyn II in the 2000 mL flexible Pharmacy Bulk Package is designed for use with manual, gravity flow operations and automated gravimetric compounding devices for preparing intravenous nutritional admixtures. Admixtures must be stored under refrigeration and used within 24 hours of admixing.

1. Peripheral Vein Nutritional Maintenance
  A mixture of Aminosyn II and dextrose diluted to a final concentration of 5% to 10% amino acids and 5% to 10% dextrose is suitable for administration by peripheral vein. This solution is not intended for central vein administration because it does not contain adequate amounts of amino acids or electrolytes.
  For peripheral intravenous infusion, 1 to 1.5 g/kg/day of total amino acids will reduce protein catabolism. Infusion or ingestion of carbohydrate or lipid will not reduce the nitrogen sparing effect of intravenous amino acid infusions at this dose.
  As with all intravenous fluid therapy, the primary aim is to provide sufficient water to compensate for insensible, urinary and other (nasogastric suction, fistula drainage, diarrhea) fluid losses. Total fluid requirements, as well as electrolyte and acid-base needs, should be estimated and appropriately administered.
  For an amino acid solution of specified total concentration, the volume required to meet amino acid requirements per 24 hours can be calculated. After making an estimate of the total daily fluid (water) requirement, the balance of fluid needed beyond the volume of amino acid solution required can be provided either as a noncarbohydrate or a carbohydrate-containing electrolyte solution. I.V. lipid emulsion may be substituted for part of the carbohydrate-containing solution. Vitamins and additional electrolytes as needed for maintenance or to correct imbalances may be added to the amino acid solution.
  If desired, only one-half of an estimated daily amino acid requirement of 1.5 g/kg can be given on the first day. Amino acids together with dextrose in concentrations of 5% to 10% infused into a peripheral vein can be continued while oral nutrition is impaired. However, if a patient is unable to take oral nourishment for a prolonged period of time, institution of total parenteral nutrition with exogenous calories should be considered.
2. Central Vein Total Parenteral Nutrition
  For central vein infusion with concentrated dextrose solution, alone or with I.V. lipid, the total daily dose of the amino acid solution depends upon daily protein requirements and the patient’s metabolic and clinical response. The determination of nitrogen balance and accurate daily body weights, corrected for fluid balance, are probably the best means of assessing individual protein requirements.

ADULTS

Solutions containing 3.5 to 5% amino acids with 5 to 10% glucose may be infused with a fat emulsion by peripheral vein to provide approximately 1400 to 2000 kcal/day. Fat emulsion administration should be considered when prolonged parenteral nutrition is required in order to prevent essential fatty acid deficiency (E.F.A.D.). Serum lipids should be monitored for evidence of E.F.A.D. in patients maintained on fat-free TPN.

Aminosyn II solution should only be infused via a central vein when admixed with sufficient dextrose to provide full caloric requirements in patients who require prolonged total parenteral nutrition. I.V. lipid may be administered to provide part of the calories, if desired. Serum lipids should be monitored for evidence of essential fatty acid deficiency in patients maintained on fat-free TPN.

Total parenteral nutrition (TPN) may be started with 10% dextrose added to the calculated daily requirement of amino acids (1.5 g/kg for a metabolically stable patient). Dextrose content is gradually increased over the next few days to the estimated daily caloric need as the patient adapts to the increasing amounts of dextrose. Each gram of dextrose provides approximately 3.4 kcal. Each gram of fat provides 9 kcal.

The average depleted major surgical patient with complications requires between 2500 and 4000 kcal and between 12 and 24 grams of nitrogen per day. An adult patient in an acceptable weight range with restricted activity who is not hypermetabolic, requires about 30 kcal/kg of body weight/day. Average daily adult fluid requirements are between 2500 and 3000 mL and may be much higher with losses from fistula drainage or severe burns. Typically, a hospitalized patient may lose 12 to 18 grams of nitrogen a day, and in severe trauma the daily loss may be 20 to 25 grams or more.

Aminosyn II solutions without electrolytes are intended for patients requiring individualized electrolyte therapy. Sodium, chloride, potassium, phosphate, calcium and magnesium are major electrolytes which should be added to Aminosyn II as required.

SERUM ELECTROLYTES SHOULD BE MONITORED AS INDICATED. Electrolytes may be added to the nutrient solution as indicated by the patient’s clinical condition and laboratory determinations of plasma values. Major electrolytes are sodium, chloride, potassium, phosphate, magnesium and calcium. Vitamins, including folic acid and vitamin K, are required additives. The trace element supplements should be given when long-term parenteral nutrition is undertaken.

Iron is added to the solution or given intramuscularly in depot form as indicated. Vitamin B12, vitamin K and folic acid are given intramuscularly or added to the solution as desired.

Calcium and phosphorus additives are potentially incompatible when added to the TPN admixture.

In patients with hyperchloremic or other metabolic acidosis, sodium and potassium may be added as the acetate or lactate salts to provide bicarbonate alternates.

In adults, hypertonic mixtures of amino acids and dextrose may be safely administered by continuous infusion through a central venous catheter with the tip located in the vena cava. Typically, each liter of central vein TPN solution for adults contains 42.5 to 50 g of Aminosyn II with approximately 250 ± 100 g of dextrose; supplementary nonprotein calories from intravenous fat emulsion may be prescribed, at the discretion of the physician.

The rate of intravenous infusion initially should be 2 mL/min and may be increased gradually. If administration should fall behind schedule, no attempt to “catch up” to planned intake should be made. In addition to meeting protein needs, the rate of administration is governed by the patient’s glucose tolerance estimated by glucose levels in blood and urine.

Aminosyn II solution, when mixed with an appropriate volume of concentrated dextrose, offers a higher concentration of calories and nitrogen per unit volume. This solution is indicated for patients requiring larger amounts of nitrogen than could otherwise be provided or where total fluid load must be kept to a minimum, for example, patients with renal failure.

Provision of adequate calories in the form of hypertonic dextrose may require exogenous insulin to prevent hyperglycemia and glycosuria. To prevent rebound hypoglycemia, do not abruptly discontinue administration of nutritional solutions.

PEDIATRIC

Pediatric requirements for parenteral nutrition are constrained by the greater relative fluid requirements of the infant and greater caloric requirements per kilogram. Amino acids are probably best administered in a 2.5% concentration. For most pediatric patients on intravenous nutrition, 2.5 grams amino acids/kg/day with dextrose alone or with I.V. lipid calories of 100 to 130 kcal/kg/day is recommended. In cases of malnutrition or stress, these requirements may be increased. It is acceptable in pediatrics to start with a nutritional solution of half strength at a rate of about 60 to 70 mL/kg/day. Within 24 to 48 hours the volume and concentration of the solution can be increased until the full strength pediatric solution (amino acids and dextrose) is given at a rate of 125 to 150 mL/kg/day.

Supplemental electrolytes and vitamin additives should be administered as deemed necessary by careful monitoring of blood chemistries and nutritional status. Addition of iron is more critical in the infant than the adult because of the increasing red cell mass required for the growing infant. Serum lipids should be monitored for evidence of essential fatty acid deficiency in patients maintained on fat-free TPN. Bicarbonate should not be administered during infusion of the nutritional solution unless deemed absolutely necessary.

To ensure the precise delivery of the small volumes of fluid necessary for total parenteral nutrition in infants, accurately calibrated and reliable infusion systems should be used. A basic solution for pediatric use should contain 25 grams of amino acids and 200 to 250 grams of glucose per 1000 mL, administered from containers containing 250 or 500 mL. Such a solution given at the rate of 145 mL/kg/day provides 130 kcal/kg/day.

Recommended Directions for Use of the Pharmacy Bulk Package

Use Aseptic Technique

1. During use, container must be stored, and all manipulations performed, in an appropriate laminar flow hood.
2. Remove cover from outlet port at bottom of container.
3. Insert piercing pin of sterile transfer set and suspend unit in a laminar flow hood. Insertion of a piercing pin into the outlet port should be performed only once in a Pharmacy Bulk Package solution. Once the outlet site has been entered, the withdrawal of container contents should be completed promptly in one continuous operation. Should this not be possible, a maximum time of 4 hours from transfer set pin or implement insertion is permitted to complete fluid transfer operations; i.e., discard container no later than 4 hours after initial closure puncture.
4. Sequentially dispense aliquots of Aminosyn II into I.V. containers using appropriate transfer set. During fluid transfer operations, the Pharmacy Bulk Package should be maintained under the storage conditions recommended in the labeling.
  Additives may be incompatible with fluid withdrawn from this container. Consult with pharmacist, if available. When compounding admixtures, use aseptic technique. Mix thoroughly. Do not store solutions containing additives. Because of the potential for life-threatening events, caution should be taken to ensure that precipitates have not formed in any parenteral nutrient mixture.

WARNING: Do not use flexible container in series connections.

HOW SUPPLIED

Aminosyn II is supplied as a Pharmacy Bulk Package in a 2000 mL flexible container for continuous admixture compounding procedures. Two concentrations are available:

Aminosyn II 10%, Sulfite-Free | NDC 0409-7172-17
Aminosyn II 10%, Sulfite-Free | NDC 0990-7172-17
Aminosyn II 15%, Sulfite-Free | NDC 0409-7171-17
Aminosyn II 15%, Sulfite-Free | NDC 0990-7171-17

ICU Medical is transitioning NDC codes from the "0409" to a "0990" labeler code. Both NDC codes are expected to be in the market for a period of time.

Store at 20 to 25°C (68 to 77°F). [See USP Controlled Room Temperature.] Protect from freezing. Avoid exposure to light.

Revised: June, 2018

EN-4657

ICU Medical, Inc., Lake Forest, Illinois, 60045, USA

PRINCIPAL DISPLAY PANEL - 2000 mL Bag Label - 7172

2000 mL
NDC 0990-7172-17
Rx ONLY

AMINOSYN™ II 10%
An Amino Acid Injection, Sulfite-Free

Pharmacy Bulk Package —
Not for Direct Infusion.

EACH 100 mL CONTAINS: TOTAL AMINO ACIDS APPROX.
10 g. MAY CONTAIN SODIUM HYDROXIDE FOR pH
ADJUSTMENT.
ESSENTIAL AMINO ACIDS/100 mL: ISOLEUCINE 660 mg;
LEUCINE 1000 mg; LYSINE (AS ACETATE SALT) 1050 mg;
METHIONINE 172 mg; PHENYLALANINE 298 mg;
THREONINE 400 mg; TRYPTOPHAN 200 mg; VALINE 500 mg.
NONESSENTIAL AMINO ACIDS/100 mL: N-ACETYL-L-
TYROSINE 270 mg; ALANINE 993 mg; ARGININE 1018 mg;
GLYCINE 500 mg; PROLINE 722 mg; HISTIDINE 300 mg;
SERINE 530 mg; L-ASPARTIC ACID 700 mg;
L-GLUTAMIC ACID 738 mg.
ELECTROLYTES (mEq/L): SODIUM 38; ACETATE 71.8.
840 mOsmol/L (ACTUAL). pH 5.8 (5.0 to 6.5) SP. GR.=1.03
FOR IV USE. USUAL DOSAGE: SEE INSERT. STERILE,
NONPYROGENIC. SEE INSERT FOR COMPLETE PRODUCT
INFORMATION FOR USE OF THE PHARMACY BULK PACKAGE.

DATE ENTERED:

TIME OF ENTRY:
CAUTION: USE ONLY IN LAMINAR FLOW HOOD. ONCE THE
OUTLET SITE HAS BEEN ENTERED, THE WITHDRAWAL OF
CONTAINER CONTENTS SHOULD BE PROMPTLY COMPLETED
IN ONE CONTINUOUS OPERATION. DISCARD CONTAINER NOT
LATER THAN 4 HOURS AFTER INITIAL CLOSURE PUNCTURE.
SEE INSERT. ADDITIVES MAY BE INCOMPATIBLE WITH
FLUID WITHDRAWN FROM THIS CONTAINER. CONSULT
WITH PHARMACIST, IF AVAILABLE. WHEN COMPOUNDING
ADMIXTURES, USE ASEPTIC TECHNIQUE. MIX THOROUGHLY.
DO NOT STORE SOLUTIONS CONTAINING ADDITIVES.
BECAUSE OF THE POTENTIAL FOR LIFE-THREATENING
EVENTS, CAUTION SHOULD BE TAKEN TO ENSURE THAT
PRECIPITATES HAVE NOT FORMED IN ANY PARENTERAL
NUTRIENT MIXTURE. STORE AT 20 to 25°C (68 to 77°F).
[SEE USP CONTROLLED ROOM TEMPERATURE.] PROTECT
FROM FREEZING. AVOID EXPOSURE TO LIGHT. USE ONLY
IF SOLUTION IS CLEAR AND CONTAINER IS UNDAMAGED.
MUST NOT BE USED IN SERIES CONNECTIONS.
THIS PRODUCT CONTAINS NO MORE THAN
25 mcg/L OF ALUMINUM.

3
V
CONTAINS DEHP

IM-4371

ICU Medical, Inc., Lake Forest, Illinois, 60045, USA

icumedical

PRINCIPAL DISPLAY PANEL - 2000 mL Bag Label - 7171

2000 mL
NDC 0990-7171-17

AMINOSYN® II
15%
An Amino Acid Injection, Sulfite-Free

Pharmacy Bulk Package—Not for Direct Infusion.

EACH 100 mL CONTAINS: TOTAL AMINO ACIDS APPROX.
15 g. MAY CONTAIN SODIUM HYDROXIDE FOR pH
ADJUSTMENT.
ESSENTIAL AMINO ACIDS/100 mL: ISOLEUCINE 990 mg;
LEUCINE 1500 mg; LYSINE (AS ACETATE SALT) 1575 mg;
METHIONINE 258 mg; PHENYLALANINE 447 mg; THREONINE
600 mg; TRYPTOPHAN 300 mg; VALINE 750 mg.
NONESSENTIAL AMINO ACIDS/100 mL: N-ACETYL-L-
TYROSINE 405 mg; ALANINE 1490 mg; ARGININE 1527 mg;
GLYCINE 750 mg; PROLINE 1083 mg; HISTIDINE 450 mg;
SERINE 795 mg; L-ASPARTIC ACID 1050 mg; L-GLUTAMIC
ACID 1107 mg.
ELECTROLYTES (mEq/LITER): SODIUM 50.0, ACETATE 107.6.
1270 mOsmol/L (ACTUAL). pH 5.8 (5.0 to 6.5) SP.GR.=1.05
FOR I.V. USE. USUAL DOSAGE: SEE INSERT. STERILE,
NONPYROGENIC. SEE INSERT FOR COMPLETE PRODUCT
INFORMATION FOR USE OF THE PHARMACY BULK PACKAGE.

DATE ENTERED:

TIME OF ENTRY:

AVOID EXPOSURE TO LIGHT.
CAUTION: USE ONLY IN LAMINAR FLOW HOOD. ONCE THE
OUTLET SITE HAS BEEN ENTERED, THE WITHDRAWAL
OF CONTAINER CONTENTS SHOULD BE PROMPTLY
COMPLETED IN ONE CONTINUOUS OPERATION. DISCARD
CONTAINER NOT LATER THAN 4 HOURS AFTER INITIAL
CLOSURE PUNCTURE. SEE INSERT. ADDITIVES MAY BE
INCOMPATIBLE WITH FLUID WITHDRAWN FROM THIS
CONTAINER. CONSULT WITH PHARMACIST, IF AVAILABLE.
WHEN COMPOUNDING ADMIXTURES, USE ASEPTIC
TECHNIQUE. MIX THOROUGHLY. DO NOT STORE SOLUTIONS
CONTAINING ADDITIVES. BECAUSE OF THE POTENTIAL FOR
LIFE-THREATENING EVENTS, CAUTION SHOULD BE TAKEN
TO ENSURE THAT PRECIPITATES HAVE NOT FORMED IN
ANY PARENTERAL NUTRIENT MIXTURE.
STORE AT 20 TO 25°C (68 TO 77°F). [SEE USP CONTROLLED
ROOM TEMPERATURE.] PROTECT FROM FREEZING.
USE ONLY IF SOLUTION IS CLEAR AND CONTAINER
IS UNDAMAGED. MUST NOT BE USED IN SERIES
CONNECTIONS.
THIS PRODUCT CONTAINS NO MORE THAN 25 mcg/L
OF ALUMINUM.

RX ONLY

3
V
CONTAINS DEHP

IM-4370

ICU Medical, Inc., Lake Forest, Illinois, 60045, USA

icumedical